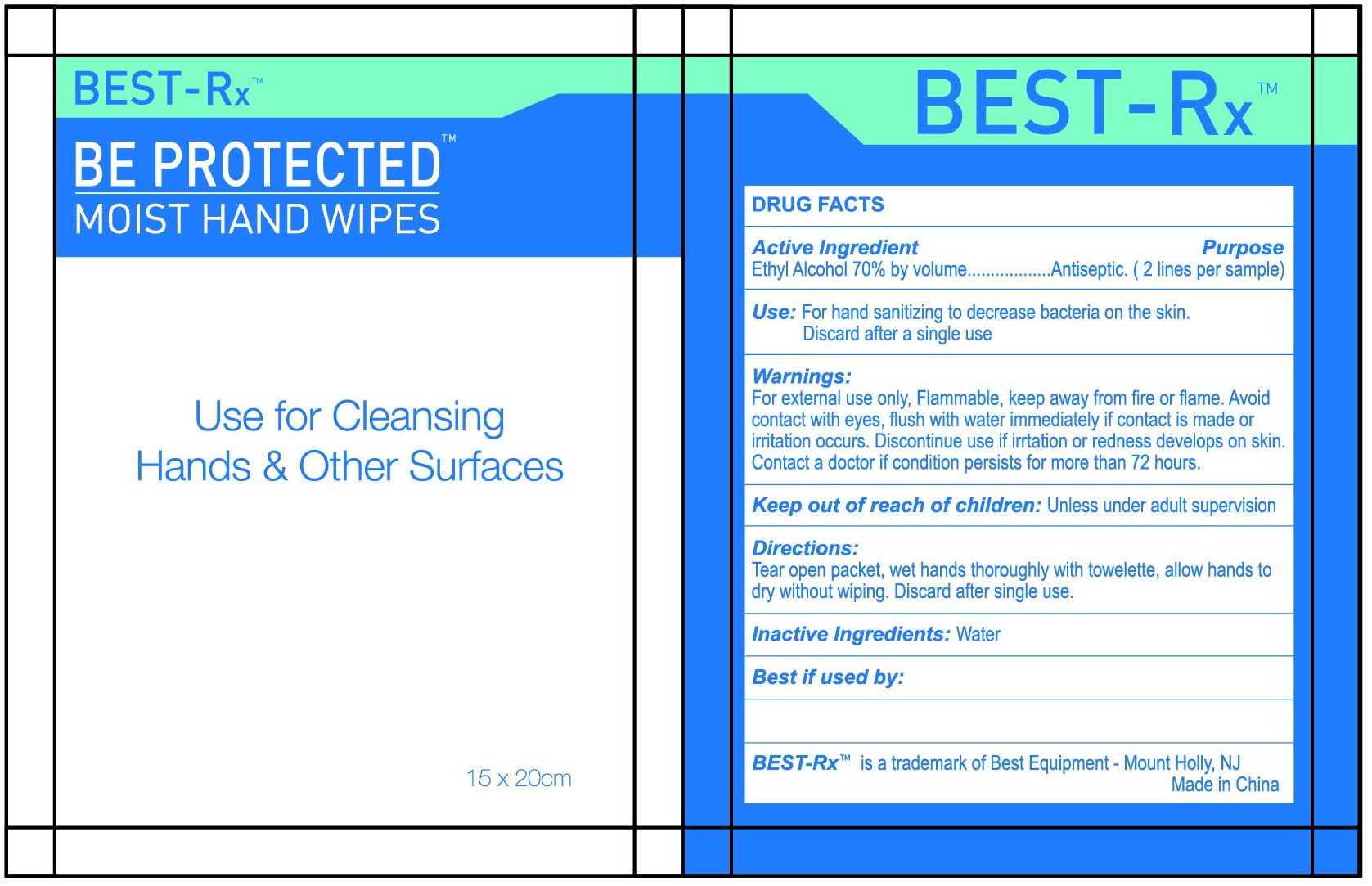 DRUG LABEL: BEST-Rx Moist Hand Wipes
NDC: 79904-001 | Form: CLOTH
Manufacturer: BEST EQUIPMENT
Category: otc | Type: HUMAN OTC DRUG LABEL
Date: 20201228

ACTIVE INGREDIENTS: ALCOHOL 0.7 U/1 U
INACTIVE INGREDIENTS: WATER

BEST-Rx Moist Hand Wipes

Active Ingredient(s)

Alcohol 70% v/v;

Purpose

Antibacterial

Use

For hand sanitizing to decrease bacterial on the skin.

Warnings

For external use only. Flammable. Keep away from heat or flame

Do not use

- on infants less than 2 months of age
- on open skin wounds

When using this product avoid contact with eyes, flush with water immediately if contact is made or irritation occurs.

STOP USE

Discontinue use if irrtation or redness develops on skin.
Contact a doctor if condition persists for more than 72 hours.

Keep out of reach of children: Unless under adult supervision.

Directions

Tear open packet, wet hands thoroughly with towelette, allow hands to dry without wiping.
Discard after single use.

Inactive ingredients

Inactive ingredients: Water

Package Label - Principal Display Panel

1 wipe in 1 pouch; NDC: 78183-001-01;